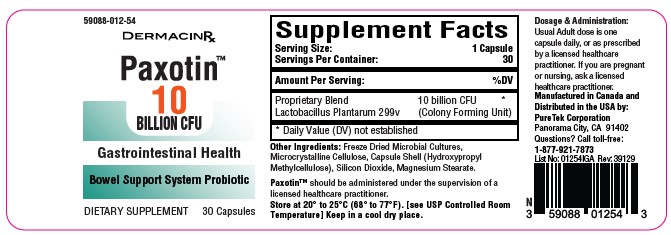 DRUG LABEL: Paxotin
NDC: 59088-012 | Form: CAPSULE
Manufacturer: PureTek Corporation
Category: other | Type: DIETARY SUPPLEMENT
Date: 20241107

ACTIVE INGREDIENTS: LACTIPLANTIBACILLUS PLANTARUM 299V 10000000000 [CFU]/1 1

Paxotin™

STATEMENT OF IDENTITY

Paxotin™

Serving Size: 1 Capsule

Servings Per Container: 30

Amount Per Serving:

Proprietary Blend: 10 billion CFU (Colony Forming Units)
Lactobacillus plantarum 299v: Identified as the specific strain included in the blend

Other Ingredients: Freeze Dried Microbial Cultures, Microcrystalline Cellulose, Capsule Shell (Hydroxypropyl Methylcellulose), Silicon Dioxide, Magnesium Stearate.
Paxotin™ should be administered under the supervision of a licensed healthcare practitioner.

DOSAGE

Usual Adult dose is one capsule daily, or as prescribed by a licensed healthcare practitioner.

If you are pregnant or nursing, ask a healthcare practitioner.

SAFE HANDLING

This product is contraindicated in patients with a known hypersensitivity to any of the ingredients.

Paxotin™ should only be used under the direction and supervision of a licensed healthcare practitioner. Use with caution in patients that may have a medical condition, are pregnant, lactating, trying to conceive, under the age of 18, or taking medications.

KEEP THIS AND ALL MEDICATIONS OUT OF THE REACH OF CHILDREN.

Do not use if bottle seal is broken.

STORAGE

Store at 20° to 25°C (68° to 77°F). [see USP Controlled Room Temperature]
Keep in a cool dry place.

HOW SUPPLIED HEALTH CLAIM

Paxotin™, Probiotic

Dietary Supplement

NHRIC: 59088-012-54 *

Bottles contain 30 Capsules

Manufactured in Canada and
Distributed in the USA by:
PureTek Corporation
Panorama City, CA 91402
Questions? Call toll-free:
1-877-921-7873

*Does not represent these product codes to be National Drug Codes (NDC). Product codes are formatted according to standard industry practice, to meet the formatting requirement by pedigree reporting and supply-chain control including pharmacies.

† The most appropriate way to ensure pedigree reporting consistent with these regulatory guidelines and safety monitoring is to dispense this product by prescription. This is not an Orange Book product. This product may be administered only under a physician’s supervision and all prescriptions using this product shall be pursuant to state statutes as applicable. The ingredients, indication or claims of this product are not to be construed to be drug claims.